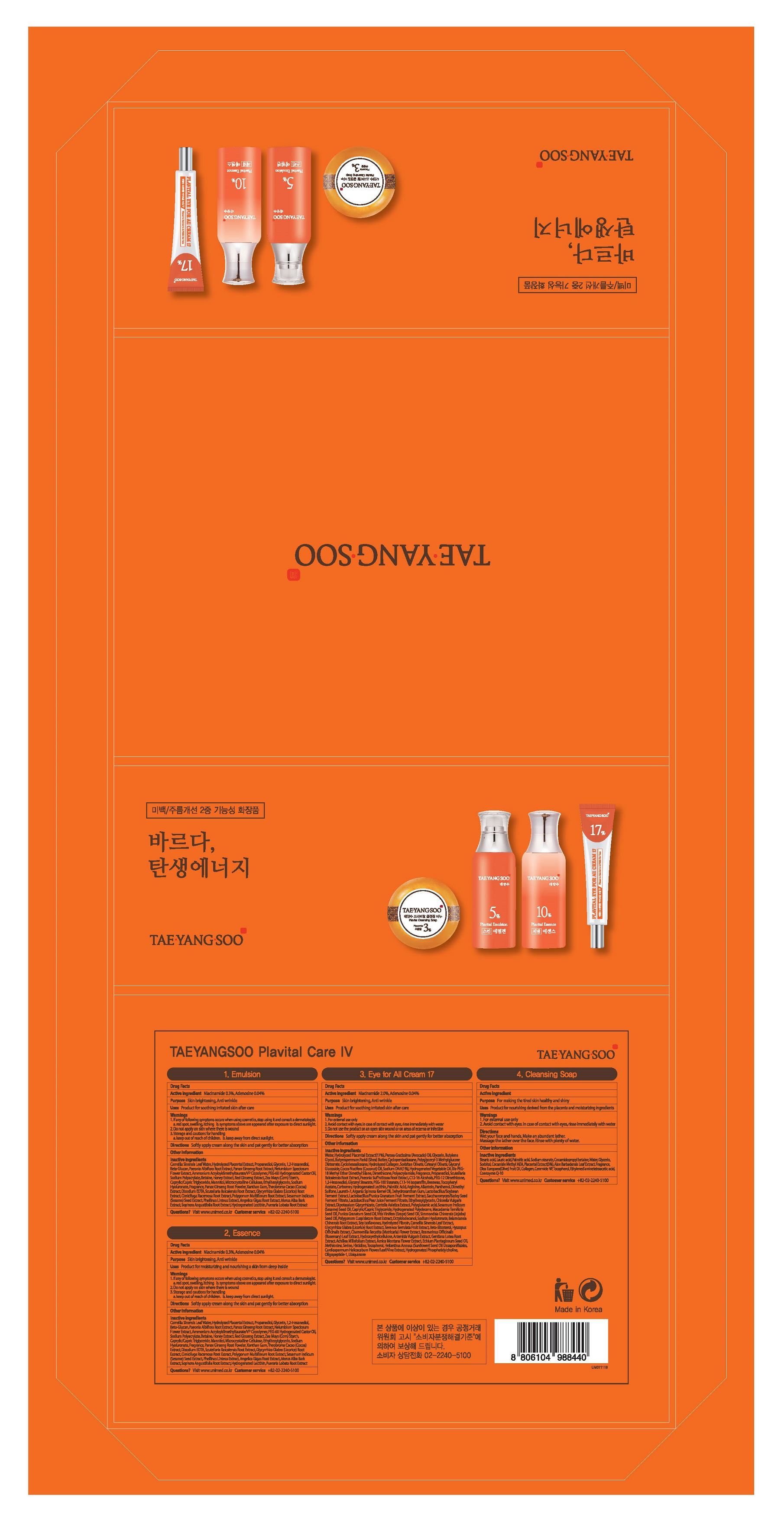 DRUG LABEL: TAEYANGSOO PlavitalEmulsion
NDC: 73669-001 | Form: EMULSION
Manufacturer: Unimed Pharmaceuticals, Inc.
Category: otc | Type: HUMAN OTC DRUG LABEL
Date: 20200927

ACTIVE INGREDIENTS: NIACINAMIDE 0.3 g/100 mL; ADENOSINE 0.04 g/100 mL
INACTIVE INGREDIENTS: WATER

Drug Facts

ACTIVE INGREDIENT

adenosine, niacinamide

INACTIVE INGREDIENT

Camellia Sinensis Leaf Water
1,2-Hexanediol
Propanediol
Water
Hydrolyzed Placental Extract
1,2-Hexanediol
Glycereth-26
Glycerin
Water
1,2-Hexanediol
Glycyrrhiza Uralensis (Licorice) Root Extract
1,2-Hexanediol
Betaine
Beta-Glucan
Water
1,2-Hexanediol
Paeonia Albiflora Root Extract
Bis-PEG-18 Methyl Ether Dimethyl Silane
Water
1,2-Hexanediol
Nelumbium Speciosum Flower Extract
PEG-60 Hydrogenated Castor Oil
Water
1,2-Hexanediol
Honey Extract
Water
1,2-Hexanediol
Portulaca Oleracea Extract
Methylpropanediol
Acrylates/C10-30 Alkyl Acrylate Crosspolymer
Arginine
Ethylhexylglycerin
Sodium Hyaluronate
Disodium EDTA
Water
Scutellaria Baicalensis Root Extract
Glycyrrhiza Glabra (Licorice) Root Extract
Cimicifuga Racemosa Root Extract
Polygonum Multiflorum Root Extract
Sesamum Indicum (Sesame) Seed Extract
Phellinus Linteus Extract
Angelica Gigas Root Extract
Morus Alba Bark Extract
Paeonia Albiflora Root Extract
Sophora Angustifolia Root Extract
1,2-Hexanediol
Phenyl Trimethicone
Fragrance

PURPOSE

anti-wrinkle, whitening

keep out of reach of the children

INDICATIONS AND USAGE

apply proper amount to the skin

WARNINGS

For external use only
When using this product

■ if the following symptoms occurs after use, stop use and consult with a skin specialist

red specks, swelling, itching

■ don’t use on the part where there is injury, eczema, or dermatitis

Keep out of reach of children

■ if swallowed, get medical help or contact a person control center immediately

DOSAGE AND ADMINISTRATION

external use only